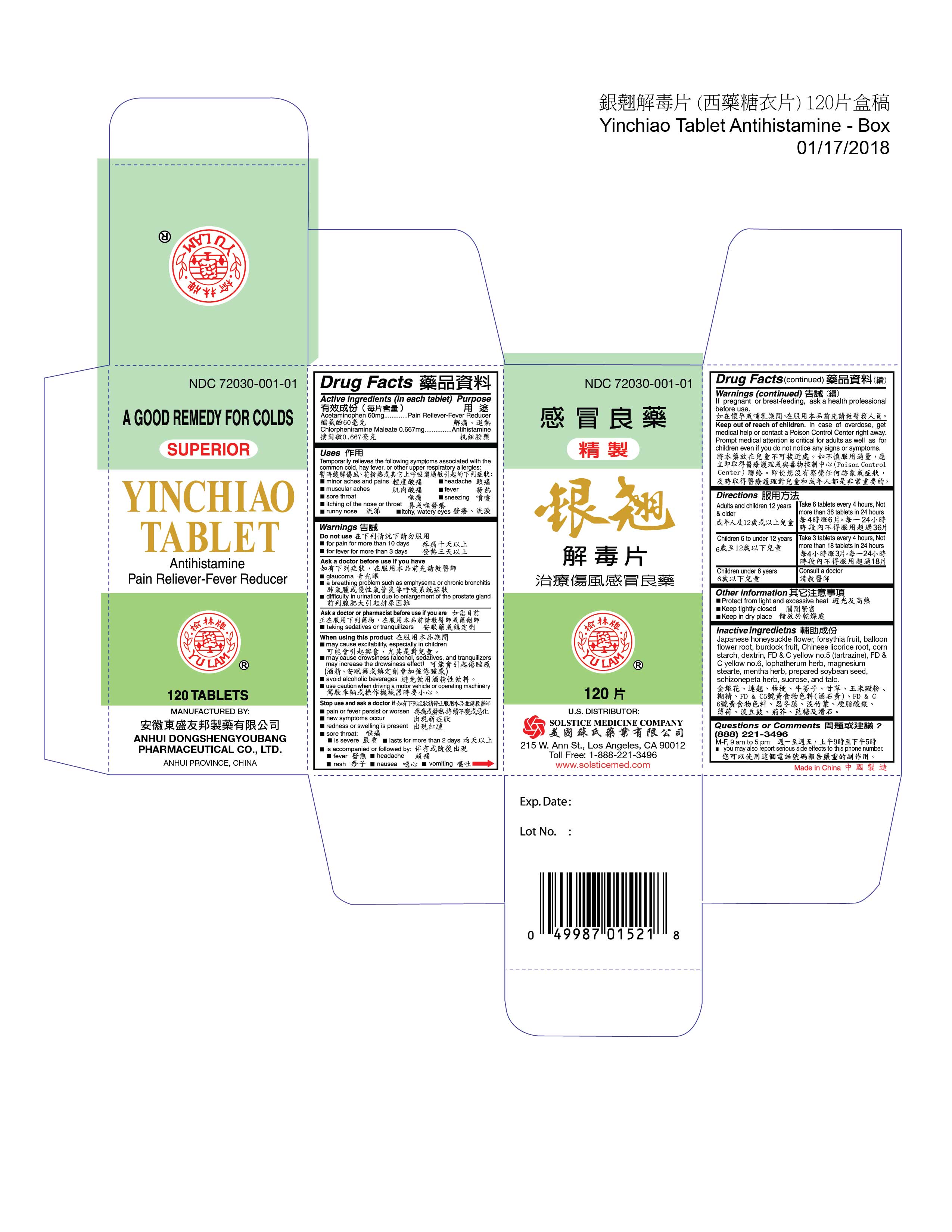 DRUG LABEL: YINCHIAO
NDC: 72030-001 | Form: TABLET, COATED
Manufacturer: ANHUI DONGSHENGYOUBANG PHARMACEUTICAL CO., LTD.
Category: otc | Type: HUMAN OTC DRUG LABEL
Date: 20251118

ACTIVE INGREDIENTS: ACETAMINOPHEN 60 mg/1 1; CHLORPHENIRAMINE MALEATE 0.667 mg/1 1
INACTIVE INGREDIENTS: LONICERA JAPONICA FLOWER; FORSYTHIA SUSPENSA FRUIT; PLATYCODON GRANDIFLORUS ROOT; ARCTIUM LAPPA FRUIT; GLYCYRRHIZA URALENSIS WHOLE; STARCH, CORN; DEXTRIN PALMITATE (CORN; 20000 MW); FD&C YELLOW NO. 5; FD&C YELLOW NO. 6; LOPHATHERUM GRACILE WHOLE; MAGNESIUM STEARATE; MINT; SOYBEAN; SCHIZONEPETA TENUFOLIA SPIKE; SUCROSE; TALC

DRUG FACTS

Active ingredient (in each tablet)
Acetaminophen 60 mg
Chlorpheniramine maleate 0.667 mg

Purpose
Pain reliever-fever reducer
Antihistamine

Uses
Temporarily relieves the following symptoms associated with the common cold, hay fever, or other upper respiratory allergies:
minor aches and pains
headache
muscular aches
fever
sore throat
sneezing
itching of the nose or throat
runny nose
itchy, watery eyes

Warnings

Do not use
for pain for more than 10 days
for fever for more than 3 days

Ask a doctor before use if the user has
glaucoma
a breathing problem such as emphysema or chronic bronchitis
difficulty in urination due to enlargement of the prostate gland

Ask a doctor or pharmacist before use if you are
taking sedatives or tranquilizers

When using this product
may cause excitability especially in children
may cause drowsiness (alcohol, sedatives, and tranquilizers may increase the drowsiness effect)
avoid alcoholic beverages
use caution when driving a motor vehicle or operating machinery

Stop use and ask a doctor if
pain or fever persists or worsen
new symptoms occur
redness or swelling is present
sore throat:
is severe
last for more than 2 days
is accompanied or followed by:
fever
headache
rash
nausea
vomiting

PREGNANCY OR BREAST FEEDING

If pregnant or breast-feeding, ask a health professional before use.

Keep out of reach of children. In case of overdose, get medical help or contact a Poison Control
Center right away. Prompt medical attention is critical for adults as well as for children even if you do
not notice any signs or symptoms.

Directions
adults and children 12 years of age and older: Take 6 tablets every 4 hours, not more than 36 tablets in 24 hours
children 6 to under 12 years of age: Take 3 tablets every 4 hours, not more than 18 tablets in 24 hours
children under 6 years: consult a doctor

Other information
protect from light our excessive heat
keep tightly closed
keep in dry place

Questions or Comments? (888) 221-3496 M-F 9 am to 5 pm
you may also use this number to report serious adverse events associated with the use of this product

Inactive ingredients
Japanese honeysuckle flower, forsythia fruit, balloon flower root, burdock fruit, Chinese licorice root, corn starch, dextrin, FD&C yellow no.5 (tartrazine), FD&C yellow no.6, lophatherum herb, magnesium stearte, mentha herb, prepared soybean seed, schizonepeta herb, sucrose, and talc.

PACKAGE LABEL

YINCHIAO TABLET, NDC 72030-001-01, Antihistamine, Pain Reliever-Fever Reducer, 120 Tablets